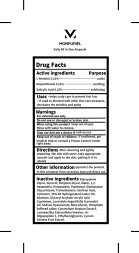 DRUG LABEL: MONPURIEL Daily all in one ample
NDC: 83472-311 | Form: LIQUID
Manufacturer: Y2K Co., Ltd.
Category: otc | Type: HUMAN OTC DRUG LABEL
Date: 20240104

ACTIVE INGREDIENTS: LEVOMENTHOL 0.33 g/100 mL; DEXPANTHENOL 0.22 g/100 mL; SALICYLIC ACID 0.25 g/100 mL
INACTIVE INGREDIENTS: LACTOBACILLUS ACIDOPHILUS; CENTELLA ASIATICA LEAF; GLYCERIN; BUTYLENE GLYCOL; WATER; PANTHENOL; GLYCYRRHIZINATE DIPOTASSIUM; TROMETHAMINE; CARBOXYPOLYMETHYLENE; ALLANTOIN; ADENOSINE; LAVENDER OIL; HYALURONATE SODIUM; GLYCERYL ACRYLATE/ACRYLIC ACID COPOLYMER (300000 CP AT 2%); SODIUM CARBOXYMETHYL .BETA.-GLUCAN (DS 0.65-0.85); LYCIUM CHINENSE FRUIT; 1,2-HEXANEDIOL; PROPANEDIOL; VINCETOXICUM ATRATUM WHOLE; NEPIDERMIN; ETHYLHEXYLGLYCERIN; SODIUM PHOSPHATE, DIBASIC, ANHYDROUS; DIPROPYLENE GLYCOL; XANTHAN GUM; PEG-60 HYDROGENATED CASTOR OIL

83472-311 MONPURIEL Daily all in one ample

Active Ingredients

L-Menthol 0.33%

Dexpanthenol 0.22%

Salicylic Acid 0.25%

Purposes

L-Menthol 0.33%-------------------------------------- coolin

Dexpanthenol 0.22%.............................................soothing

Salicylic Acid 0.25%---------------------------------- exfoliating

Uses

• helps scalp care for to prevent hair loss

• if used as directed with other skin care measures, decreases the wrinkles and aging

Warnings

For external use only

Warnings

Do not use on damaged or broken skin

Warnings

Keep out of reach of children. If swallowed, get medical help or contact a Poison Control Center right away.

Warnings

Stop use and ask a doctor if rash occurs

Warnings

When using this product keep out of eyes.

Directions

After cleansing and lightly preparing the skin with toner, take appropriate amount and apply to the skin, patting it in to absorb

Inactive Ingredients

Dipropylene Glycol, Glycerin, Butylene Glycol, Water, 1,2-Hexanediol, Propanediol, Panthenol, Dipotassium Glycyrrhizate, Tromethamine, Xanthan Gum, Carbomer, PEG-60 Hydrogenated Castor Oil, Allantoin, Adenosine,

Glyceryl Acrylate/Acrylic Acid Copolymer, Lavandula Angustifolia (Lavender) Oil (Allergens : Geraniol, Limonene, Linalool),

Sodium Hyaluronate, Beta-Glucan, Phosphate buffered saline, Cynanchum Atratum Extract, Lactobacillus Extracellular Vesicles,

sh-Oligopeptide-1, Ethylhexylglycerin, Lycium Chinense Fruit Extract